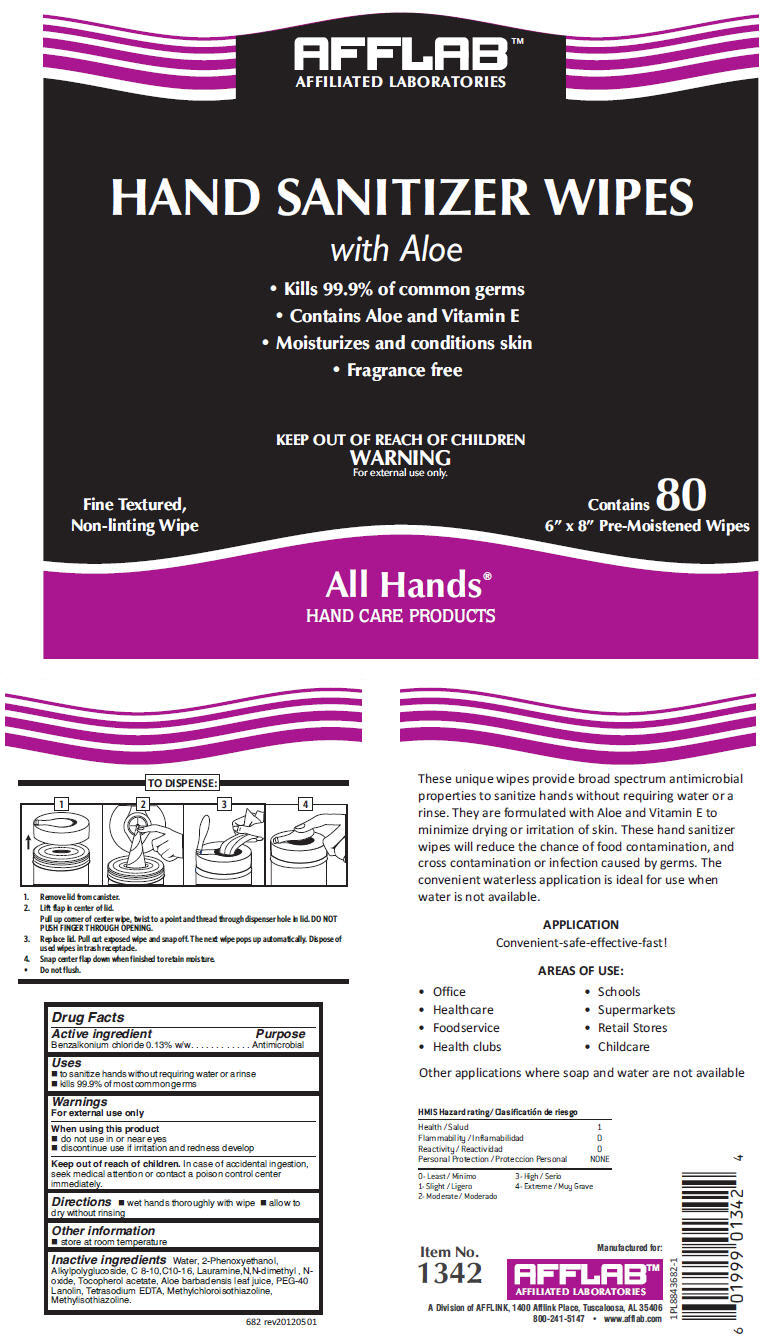 DRUG LABEL: Hand Sanitizer Wipes with Aloe
NDC: 54057-682 | Form: CLOTH
Manufacturer: AFFLABS, Affiliated Laboratories, A Division of AFFLINK
Category: otc | Type: HUMAN OTC DRUG LABEL
Date: 20121107

ACTIVE INGREDIENTS: BENZALKONIUM CHLORIDE 0.0067275 g/1 1
INACTIVE INGREDIENTS: Water; phenoxyethanol; Decyl Glucoside; Lauramine Oxide; .Alpha.-Tocopherol Acetate; Aloe Vera Leaf; Edetate Sodium; Methylchloroisothiazolinone; Methylisothiazolinone

Hand Sanitizer Wipes with Aloe

Drug Facts

Active ingredient

Benzalkonium chloride 0.13% w/w

Purpose

Antimicrobial

Uses

- to sanitize hands without requiring water or a rinse
- kills 99.9% of most common germs

Warnings

For external use only

When using this product

- do not use in or near eyes
- discontinue use if irritation and redness develop

Keep out of reach of children. In case of accidental ingestion, seek medical attention or contact a poison control center immediately.

Directions

- wet hands thoroughly with wipe
- allow to dry without rinsing

Other information

- store at room temperature

Inactive ingredients

Water, 2-Phenoxyethanol, Alkylpolyglucoside, C 8-10,C10-16, Lauramine,N,N-dimethyl , N-oxide, Tocopherol acetate, Aloe barbadensis leaf juice, PEG-40 Lanolin, Tetrasodium EDTA, Methylchloroisothiazoline, Methylisothiazoline.

Manufactured for:
AFFLAB™
AFFILIATED LABORATORIES
A Division of AFFLINK, 1400 Afflink Place, Tuscaloosa, AL 35406

PRINCIPAL DISPLAY PANEL - 80 Count Canister

AFFLAB™
AFFILIATED LABORATORIES

HAND SANITIZER WIPES

with Aloe

- Kills 99.9% of common germs
- Contains Aloe and Vitamin E
- Moisturizes and conditions skin
- Fragrance free

KEEP OUT OF REACH OF CHILDREN
WARNING
For external use only.

Fine Textured,
Non-linting Wipe

Contains 80
6" x 8" Pre-Moistened Wipes

All Hands®
HAND CARE PRODUCTS